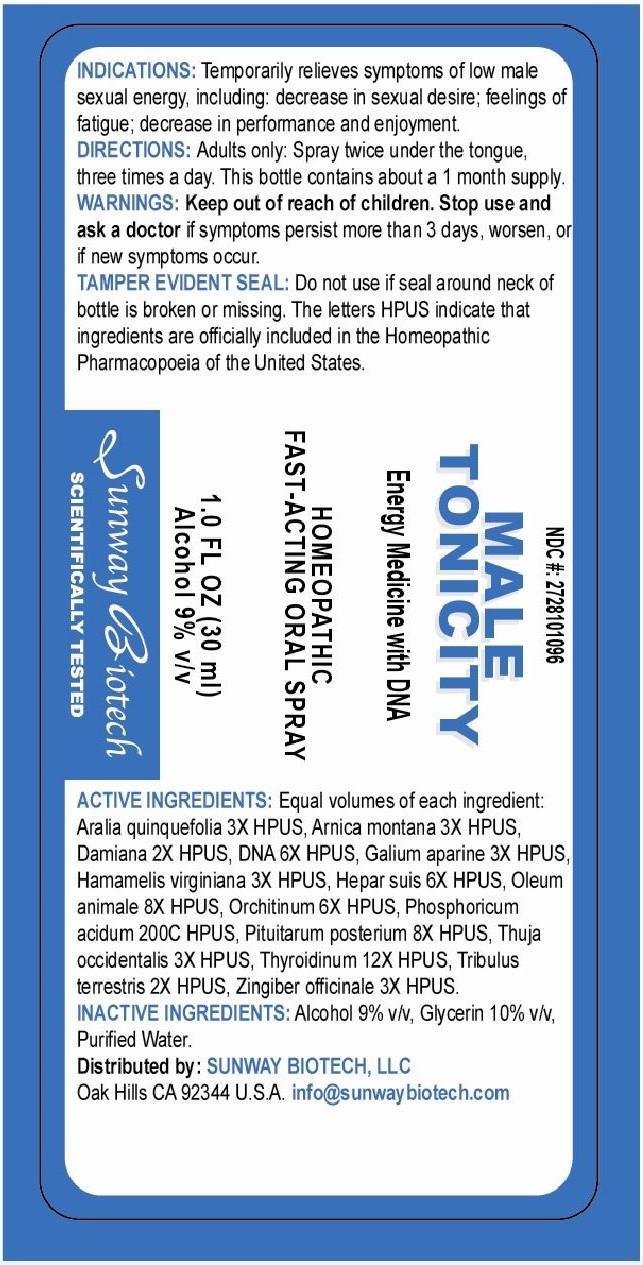 DRUG LABEL: Male Tonicity
NDC: 27281-010 | Form: SPRAY
Manufacturer: Sunway Biotech LLC
Category: homeopathic | Type: HUMAN OTC DRUG LABEL
Date: 20140808

ACTIVE INGREDIENTS: AMERICAN GINSENG 1.5 [hp_C]/1 mg; ARNICA MONTANA 1.5 [hp_C]/1 mg; TURNERA DIFFUSA LEAFY TWIG 1 [hp_C]/1 mg; HERRING SPERM DNA 3 [hp_C]/1 mg; GALIUM APARINE 1.5 [hp_C]/1 mg; HAMAMELIS VIRGINIANA ROOT BARK/STEM BARK 1.5 [hp_C]/1 mg; PORK LIVER 3 [hp_C]/1 mg; CERVUS ELAPHUS HORN OIL 4 [hp_C]/1 mg; OVIS ARIES TESTICLE 3 [hp_C]/1 mg; PHOSPHORIC ACID 200 [hp_C]/1 mg; SUS SCROFA PITUITARY GLAND 4 [hp_C]/1 mg; THUJA OCCIDENTALIS LEAFY TWIG 1.5 [hp_C]/1 mg; THYROID, UNSPECIFIED 6 [hp_C]/1 mg; TRIBULUS TERRESTRIS 1 [hp_C]/1 mg; GINGER 1.5 [hp_C]/1 mg
INACTIVE INGREDIENTS: ALCOHOL; GLYCERIN; WATER

Active Ingredients: Equal volumes of each ingredient:

aralia quinquefolia 3X HPUS, arnica montana 3X HPUS, damiana 2X HPUS, DNA 6X HPUS, galium aparine 3X HPUS, hamamelis virginiana 3X HPUS, hepar suis 6X HPUS, oleum animale 8X HPUS, orchitinum 6X HPUS, phosphoricum acidum 200C HPUS, pituitarium posterium 8X HPUS, thuja occidentalis 3X HPUS, thyroidinum 12X HPUS, tribulus terrestris 2X HPUS, zingiber officinale 3X HPUS.

PURPOSE

Male Tonicity

Energy Medicine with DNA

Homeopathic Fast-Acting Oral Spray

1.0 Fl Oz (30 ml)

Alcohol 9% v/v

Sunway Biotech

Scientifically Tested

Keep out of reach of children.

DOSAGE AND ADMINISTRATION

Directions: Adults Only: Spray twice under the tongue, three times a day. This bottle contains about a 1 month supply.

WARNINGS

Warnings: Stop use and ask a doctor if symptoms persist more than 3 days, worsen, or if new symptoms occur.

Tamper Evident Seal: Do not use if seal around neck of bottle is broken or missing. The letters HPUS indicate that ingredients are officially included in the Homeopathic Pharmacopoeia of the United States.

INDICATIONS AND USAGE

Indications: Temporarily relieves symptoms of low male sexual energy, including: decrease in sexual desire; feelings of fatigue; decrease in performance and enjoyment.

INACTIVE INGREDIENT

Inactive Ingredients: alcohol 9% v/v, glycerin 10% v/v, purified water.